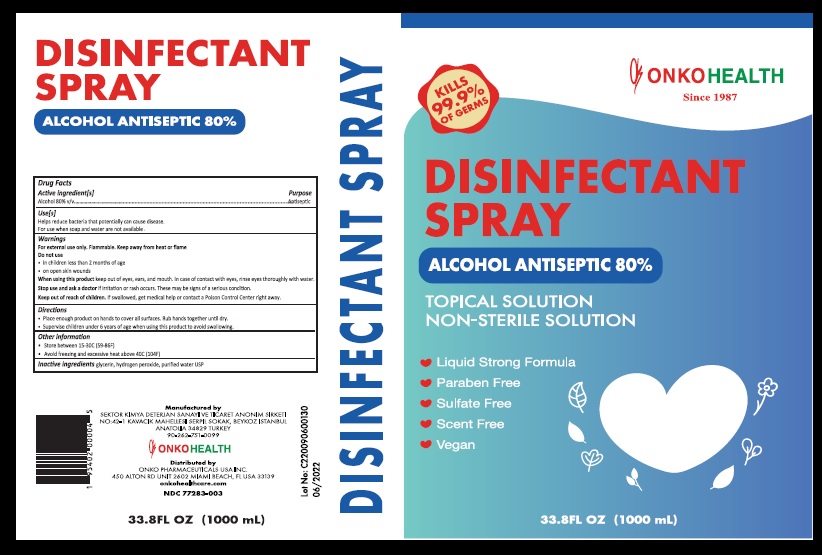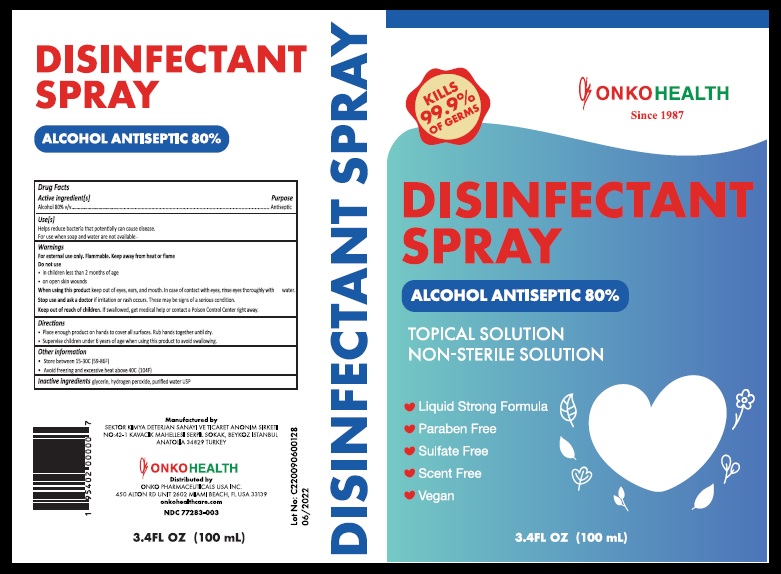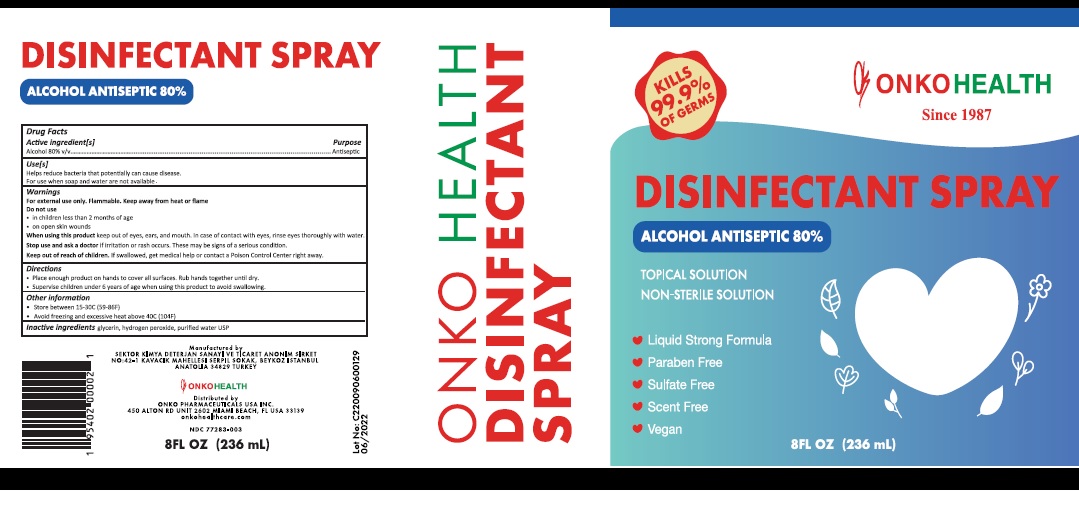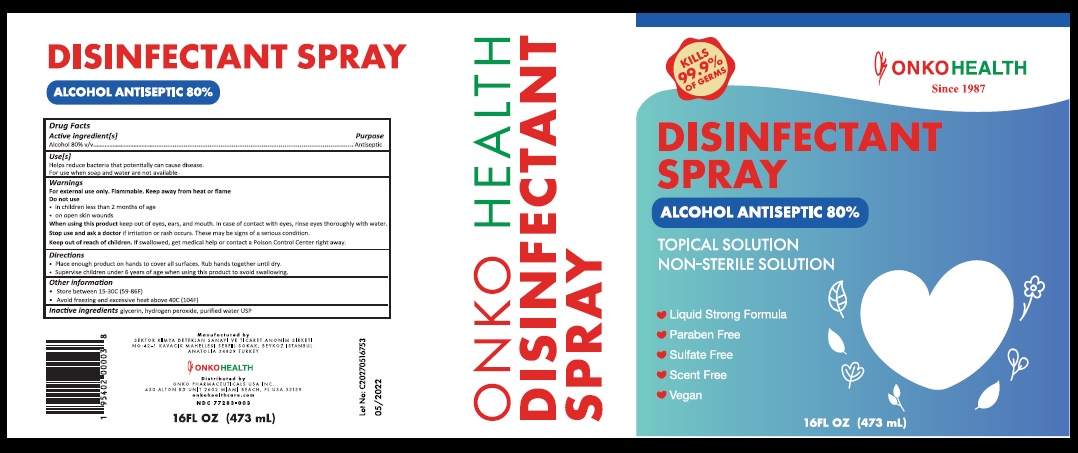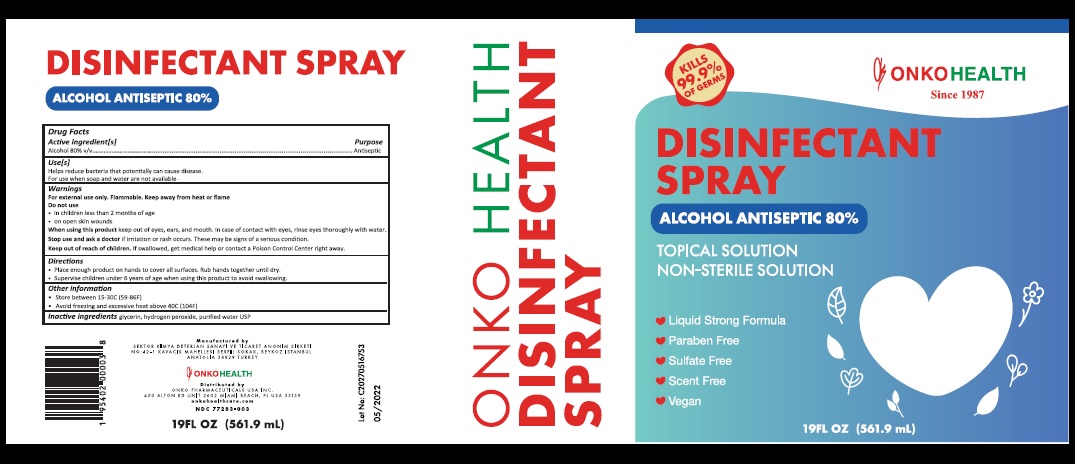 DRUG LABEL: ONKO HEALTH
NDC: 77283-003 | Form: LIQUID
Manufacturer: ONKO PHARMACEUTICALS USA INC
Category: otc | Type: HUMAN OTC DRUG LABEL
Date: 20210119

ACTIVE INGREDIENTS: ALCOHOL 80 mL/100 mL
INACTIVE INGREDIENTS: GLYCERIN; HYDROGEN PEROXIDE; WATER

ONKO HEALTH
DISINFECTANT SPRAY

Active Ingredients

Alcohol 80%

Purposes

Antiseptic.

Uses

· Helps reduce bacteria that potentially can cause disease.

· For use when soap and water are not available.

Warnings

For external use only. Flammable. Keep away from heat or flame
Do not use

- In children less than 2 months of age
- On open skin wounds
- When using this product keep out of eyes, ears, and mouth. In case of contact with eyes, rinse eyes thoroughly with water.

- Stop use and ask a doctor if irritation or rash occurs. These may be signs of a serious condition.

Directions

- Place enough product on hands to cover all surfaces. Rub hands together until dry.
- Supervise children under 6 years of age when using this product to avoid swallowing

Keep out of reach of children

If swallowed, get medical help or contact a Poison Control Center right away.

Other Information

- Store between 15-30C (59-86F)

● Avoid freezing and excessive heat above 40C (104F)

Inactive Ingredients

Glycerin, hydrogen peroxide, purified water USP